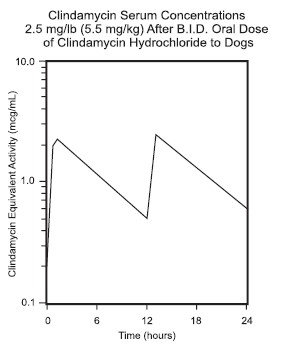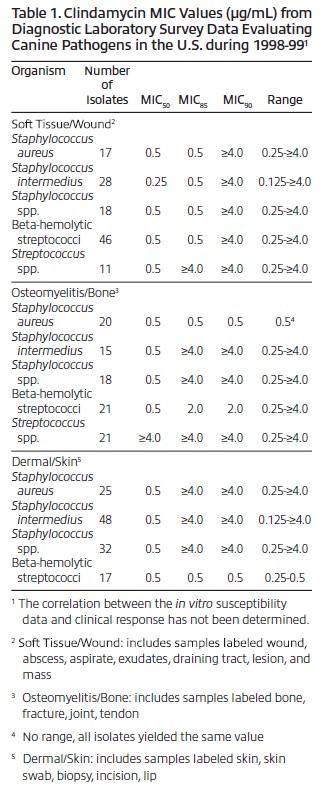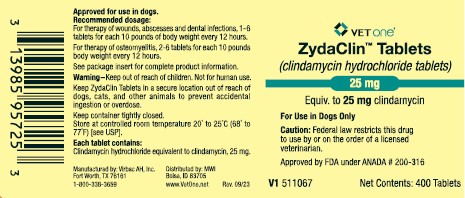 DRUG LABEL: ZydaClin
NDC: 13985-957 | Form: TABLET
Manufacturer: VetOne
Category: animal | Type: PRESCRIPTION ANIMAL DRUG LABEL
Date: 20240226

ACTIVE INGREDIENTS: clindamycin hydrochloride 25 mg/1 1

ZydaClin™ Tablets (clindamycin hydrochloride tablets)

CAUTION:

Federal law restricts this drug to use by or on the order of a licensed veterinarian.

DESCRIPTION

ZydaClin™ Tablets contain clindamycin hydrochloride which is the hydrated salt of clindamycin. Clindamycin is a semisynthetic antibiotic produced by a 7(S)-chlorosubstitution of the 7(R)-hydroxyl group of a naturally produced antibiotic produced by Streptomyces lincolnensis var. lincolnensis.

ZydaClin Tablets (For Use in Dogs Only): 25 mg Tablet, each white bisected tablet is marked “C” above the bisect and “25” below the bisect and contains clindamycin hydrochloride equivalent to 25 mg of clindamycin.

CLINICAL PHARMACOLOGY

Absorption: Clindamycin hydrochloride is rapidly absorbed from the canine gastrointestinal tract.

Dog Serum Levels: Serum levels at or above 0.5 μg/mL can be maintained by oral dosing at a rate of 2.5 mg/lb of clindamycin hydrochloride every 12 hours. This same study revealed that average peak serum concentrations of clindamycin occur 1 hour and 15 minutes after oral dosing. The elimination half-life for clindamycin in dog serum was approximately 5 hours. There was no bioactivity accumulation after a regimen of multiple oral doses in healthy dogs.

Metabolism and Excretion: Extensive studies of the metabolism and excretion of clindamycin hydrochloride administered orally in animals and humans have shown that unchanged drug and bioactive and bioinactive metabolites are excreted in urine and feces. Almost all of the bioactivity detected in serum after clindamycin hydrochloride administration is due to the parent molecule (clindamycin). Urine bioactivity, however, reflects a mixture of clindamycin and active metabolites, especially N-demethyl clindamycin and clindamycin sulfoxide.

Site and Mode of Action: Clindamycin is an inhibitor of protein synthesis in the bacterial cell. The site of binding appears to be in the 50S sub-unit of the ribosome. Binding occurs to the soluble RNA fraction of certain ribosomes, thereby inhibiting the binding of amino acids to those ribosomes. Clindamycin differs from cell wall inhibitors in that it causes irreversible modification of the proteinsynthesizing subcellular elements at the ribosomal level.

Microbiology: Clindamycin is a lincosaminide antimicrobial agent with activity against a wide variety of aerobic and anaerobic bacterial pathogens. Clindamycin is a bacteriostatic compound that inhibits bacterial protein synthesis by binding to the 50S ribosomal sub-unit. The minimum inhibitory concentrations (MICs) of Gram-positive and obligate anaerobic pathogens isolated from dogs in the United States are presented in Table 1. Bacteria were isolated in 1998-1999. All MICs were performed in accordance with the Clinical and Laboratory Standards Institute (CLSI).

INDICATIONS

ZydaClin™ Tablets (clindamycin hydrochloride tablets) (for use in dogs only) are indicated for the treatment of infections caused by susceptible strains of the designated microorganisms in the specific conditions listed below:

Dogs: Skin infections (wounds and abscesses) due to: coagulase positive staphylococci (Staphylococcus aureus or Staphylococcus intermedius).

Deep wounds and abscesses due to Bateroides fragilis, Prevotella melaninogenicus, Fusobacterium necrophorum and Clostridium perfringens.

Dental infections due to Staphyloccus aureus, Bacteroides fragilis, Prevotella melaninogenicus, Fusobacterium necrophorum and Clostridium perfringens.

Osteomyelitis due to Staphylococcus aureus, Bacteroides fragilis, Prevotella melaninogenicus, Fusobacterium necrophorum and Clostridium perfringens.

CONTRAINDICATIONS

ZydaClin Tablets are contraindicated in animals with a history of hypersensitivity to preparations containing clindamycin or lincomycin.

Because of potential adverse gastrointestinal effects, do not administer to rabbits, hamsters, guinea pigs, horses, chinchillas or ruminating animals.

WARNINGS

Keep out of reach of children. Not for human use.

Keep ZydaClin Tablets in a secure location out of reach of dogs, cats, and other animals to prevent accidental ingestion or overdose.

PRECAUTIONS

During prolonged therapy of one month or greater, periodic liver and kidney function tests and blood counts should be performed.

The use of clindamycin hydrochloride occasionally results in overgrowth of non-susceptible organisms such as clostridia and yeasts. Therefore, the administration of ZydaClin Tablets should be avoided in those species sensitive to the gastrointestinal effects of clindamycin (see CONTRAINDICATIONS). Should superinfections occur, appropriate measures should be taken as indicated by the clinical situation.

Patients with very severe renal disease and/or very severe hepatic disease accompanied by severe metabolic aberrations should be dosed with caution, and serum clindamycin levels monitored during high-dose therapy.

Clindamycin hydrochloride has been shown to have neuromuscular blocking properties that may enhance the action of other neuromuscular blocking agents. Therefore, ZydaClin Tablets should be used with caution in animals receiving such agents.

Safety in gestating bitches or breeding male dogs has not been established.

ADVERSE REACTIONS

Side effects occasionally observed in either clinical trials or during clinical use were vomiting and diarrhea.

To report adverse reactions or a suspected adverse reaction, call 1-800-338-3659.

DOSAGE AND ADMINISTRATION

Dogs:
Infected Wounds, Abscesses, and Dental Infections

Oral: 2.5-15.0 mg/lb body weight every 12 hours.

Duration: Treatment with clindamycin hydrochloride products may be continued up to a maximum of 28 days if clinical judgment indicates. Treatment of acute infections should not be continued for more than three or four days if no response to therapy is seen.

Dosage Schedule:
Tablets
ZydaClin Tablets 25 mg, administer 1-6 tablets every 12 hours for each 10 pounds of body weight.

Dogs:
Osteomyelitis
Oral: 5.0-15.0 mg/lb body weight every 12 hours.
Duration: Treatment with clindamycin hydrochloride is recommended for a minimum of 28 days. Treatment should not be continued for longer than 28 days if no response to therapy is seen.

Dosage Schedule:
Tablets
ZydaClin Tablets 25 mg, administer 2-6 tablets every 12 hours for each 10 pounds of body weight.

ANIMAL SAFETY SUMMARY

Rat and Dog Data: One year oral toxicity studies in rats and dogs at doses of 30, 100 and 300 mg/kg/day (13.6, 45.5 and 136.4 mg/lb/day) have shown clindamycin hydrochloride capsules to be well tolerated. Differences did not occur in the parameters evaluated to assess toxicity
when comparing groups of treated animals with contemporary controls. Rats administered clindamycin hydrochloride at 600 mg/kg/day (272.7 mg/lb/day) for six months tolerated the drug well; however, dogs orally dosed at 600 mg/kg/day (272.7 mg/lb/day) vomited, had anorexia, and subsequently lost weight. At necropsy these dogs had erosive gastritis and focal areas of necrosis of the mucosa of the gall bladder.

Safety in gestating bitches or breeding males has not been established.

STORAGE

Store at controlled room temperature 20˚ to 25˚ C (68˚ to 77˚ F) [see USP].

HOW SUPPLIED

ZydaClin Tablets are available as:
25 mg - bottles of 400

Approved by FDA under ANADA # 200-316

To report suspected adverse drug events, for technical assistance or to obtain a copy of the Safety Data Sheet (SDS), contact Virbac AH, Inc. at 1-800-338-3659 or us.virbac.com. For additional information about adverse drug experience reporting for animal drugs, contact FDA at 1-888-FDA-VETS or http://www.fda.gov/reportanimalae.

Distributed by: MWI

Boise, ID 83705

www.VetOne.net Rev.: 10/23 302276-02